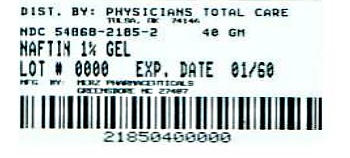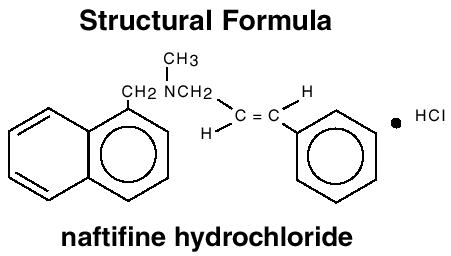 DRUG LABEL: Naftin
NDC: 54868-2185 | Form: GEL
Manufacturer: Physicians Total Care, Inc.
Category: prescription | Type: HUMAN PRESCRIPTION DRUG LABEL
Date: 20130304

ACTIVE INGREDIENTS: NAFTIFINE HYDROCHLORIDE 10 mg/1 g
INACTIVE INGREDIENTS: POLYSORBATE 80; CARBOMER 934; DIISOPROPANOLAMINE; EDETATE DISODIUM

NAFTIN®
NAFTIFINE HCl 1% GEL

Rx Only

DESCRIPTION

Naftin® Gel, 1% contains the synthetic, broad-spectrum, antifungal agent naftifine hydrochloride. Naftin® Gel, 1% is for topical use only.

Chemical Name

(E)-N-Cinnamyl-N-methyl-1-naphthalenemethylamine hydrochloride.

Naftifine hydrochloride has an empirical formula of C21H21N•HCl and a molecular weight of 323.86.

Contains

Active Ingredient
Naftifine hydrochloride | 1%

Inactive Ingredients
polysorbate 80, carbomer 934P, diisopropanolamine, edetate disodium, alcohol (52%v/v) and purified water.

CLINICAL PHARMACOLOGY

Naftifine hydrochloride is a synthetic allylamine derivative. The following in vitro data are available, but their clinical significance is unknown. Naftifine hydrochloride has been shown to exhibit fungicidal activity in vitro against a broad spectrum of organisms, including Trichophyton rubrum, Trichophyton mentagrophytes, Trichophyton tonsurans, Epidermophyton floccosum, Microsporum canis, Microsporum audouini, and Microsporum gypseum; and fungistatic activity against Candida species, including Candida albicans. Naftin® Gel, 1% has only been shown to be clinically effective against the disease entities listed in the INDICATIONS AND USAGE section.

Although the exact mechanism of action against fungi is not known, naftifine hydrochloride appears to interfere with sterol biosynthesis by inhibiting the enzyme squalene 2, 3-epoxidase. This inhibition of enzyme activity results in decreased amounts of sterols, especially ergosterol, and a corresponding accumulation of squalene in the cells.

Pharmacokinetics

In vitro and in vivo bioavailability studies have demonstrated that naftifine penetrates the stratum corneum in sufficient concentration to inhibit the growth of dermatophytes.

Following single topical applications of ^3H-labeled naftifine gel 1% to the skin of healthy subjects, up to 4.2% of the applied dose was absorbed. Naftifine and/or its metabolites are excreted via the urine and feces with a half-life of approximately two to three days.

INDICATIONS AND USAGE

Naftin® Gel, 1% is indicated for the topical treatment of tinea pedis, tinea cruris and tinea corporis caused by the organisms Trichophyton rubrum, Trichophyton mentagrophytes, Trichophyton tonsurans [Efficacy for this organism in this organ system was studied in fewer than 10 infections.] and Epidermophyton floccosum.

CONTRAINDICATIONS

Naftin® Gel, 1% is contraindicated in individuals who have shown hypersensitivity to any of its components.

WARNINGS

Naftin® Gel, 1% is for topical use only and not for ophthalmic use.

PRECAUTIONS

General

Naftin® Gel, 1% is for external use only. If irritation or sensitivity develops with the use of Naftin® Gel, 1%, treatment should be discontinued and appropriate therapy instituted. Diagnosis of the disease should be confirmed either by direct microscopic examination of a mounting of infected tissue in a solution of potassium hydroxide or by culture on an appropriate medium.

Information for patients

The patient should be told to:

1. Avoid the use of occlusive dressings or wrappings unless otherwise directed by the physician.
2. Keep Naftin® Gel, 1% away from the eyes, nose, mouth and other mucous membranes.

Carcinogenesis, mutagenesis, impairment of fertility

Long-term studies to evaluate the carcinogenic potential of Naftin® Gel, 1% have not been performed. In vitro and animal studies have not demonstrated any mutagenic effect or effect on fertility.

Pregnancy

Teratogenic Effects

Pregnancy Category B

Reproduction studies have been performed in rats and rabbits (via oral administration) at doses 150 times or more than the topical human dose and have revealed no evidence of impaired fertility or harm to the fetus due to naftifine. There are, however, no adequate and well-controlled studies in pregnant women. Because animal reproduction studies are not always predictive of human response, this drug should be used during pregnancy only if clearly needed.

Nursing mothers

It is not known whether this drug is excreted in human milk. Because many drugs are excreted in human milk, caution should be exercised when Naftin® Gel, 1% is administered to a nursing woman.

Pediatric use

Safety and effectiveness in pediatric patients have not been established.

ADVERSE REACTIONS

During clinical trials with Naftin® Gel, 1%, the incidence of adverse reactions was as follows: burning/stinging (5.0%), itching (1.0%), erythema (0.5%), rash (0.5%), skin tenderness (0.5%).

DOSAGE AND ADMINISTRATION

A sufficient quantity of Naftin® Gel, 1% should be gently massaged into the affected and surrounding skin areas twice a day in the morning and evening. The hands should be washed after application.

If no clinical improvement is seen after four weeks of treatment with Naftin® Gel, 1%, the patient should be re-evaluated.

HOW SUPPLIED

Naftin® (naftifine hydrochloride) 1% Gel is supplied in collapsible tubes in the following sizes:

40 gram | NDC 54868-2185-2

STORAGE AND HANDLING

Note: Store at room temperature.

Manufactured for: Merz Pharmaceuticals, Greensboro, NC 27410

5011343
© 2009 Merz Pharmaceuticals
Rev 2/09 Printed in U.S.A.

Relabeling of "Additional Barcode" by:
Physicians Total Care, Inc.
Tulsa, OK 74146

PRINCIPAL DISPLAY PANEL

NAFTIN®

NAFTIFINE HCl 1% GEL

Rx Only